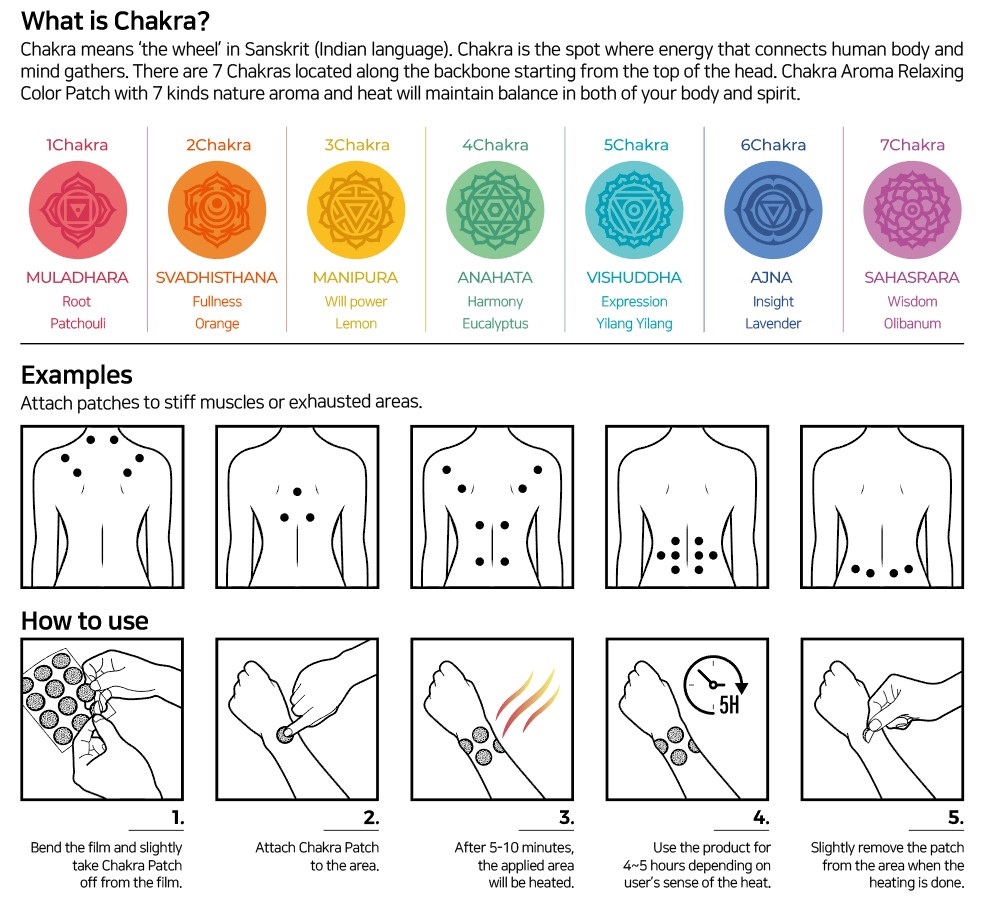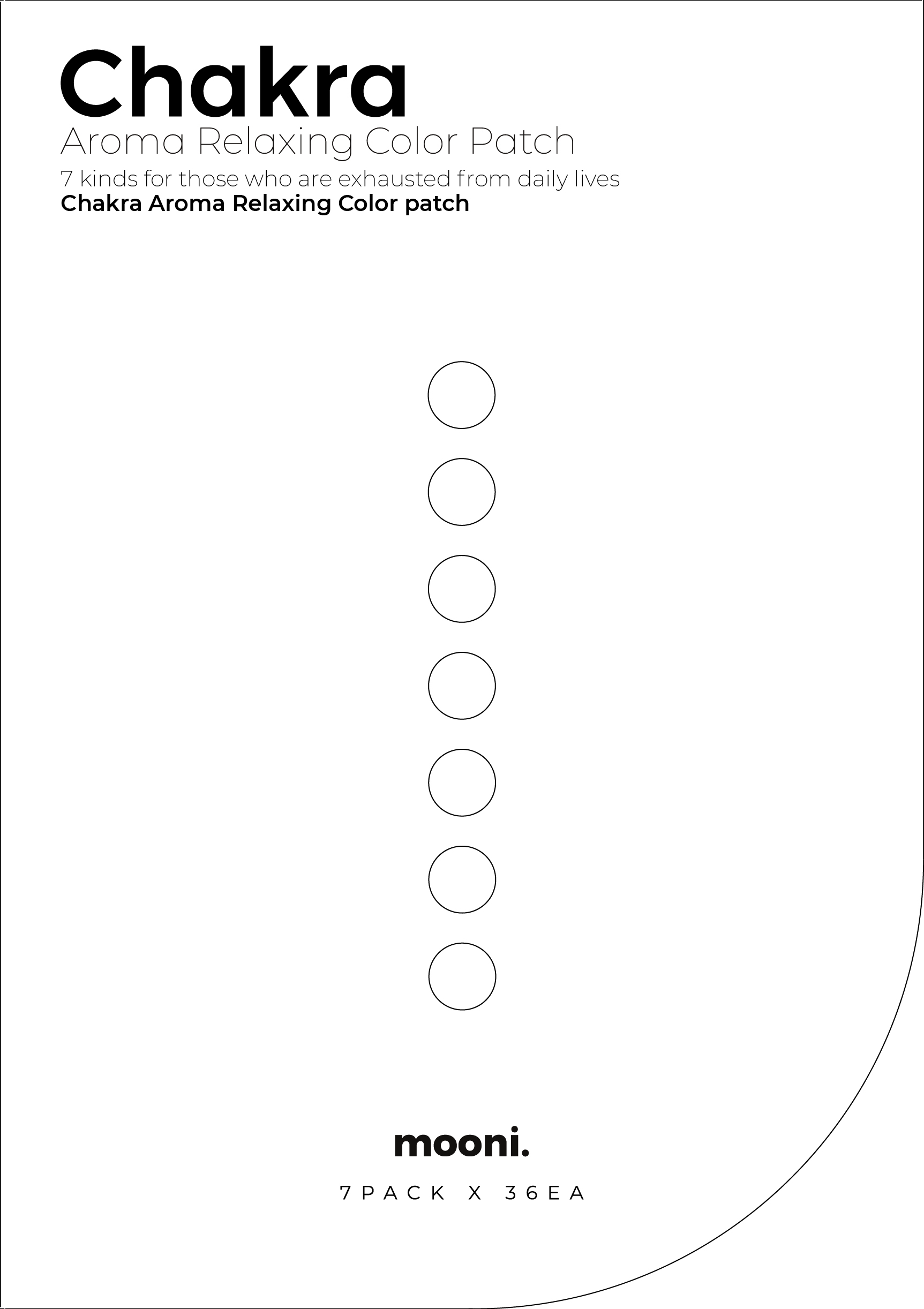 DRUG LABEL: Chakra Aroma Relaxing Color
NDC: 72880-0100 | Form: PATCH
Manufacturer: mooni studio
Category: otc | Type: HUMAN OTC DRUG LABEL
Date: 20190219

ACTIVE INGREDIENTS: CAPSICUM OLEORESIN 0.2 g/1 1
INACTIVE INGREDIENTS: GLYCERIN; 1,2-HEXANEDIOL; SILVER

Drug Facts

Active ingredients

CAPSICUM OLEORESIN

Inactive ingredients

Styrene isoprene rubber, silver powder, 1,2-hexandiol, 2hydroxy benzoic acid, glycerin, hydrogenated hydrocabon resin, aroma oil (patchouli oil, orange oil, lemon oil, eucalyptus oil, ylang-ylang oil, lavender oil, olibanum oil)

Purposes

Topical analgesic

Warnings

- It is normal that the product heats the attached area, but if a rash appears on the skin, stop using the product immediately and go to see a doctor.

- Those who have sensitive skin or dermatitis should avoid long-hour usage(over 5 hours).

- Be careful using the product before or after sauna and hot massage when your skin may be more sensitive than the usual.

- If you feel itchy, remove the patch immediately and wash off the area with cold water.

- Do NOT use the product during pregnancy.

- Do NOT use the product to infants/children under 30 months.

- This product is NOT a medicine, but one of the manufactured goods

DOSAGE AND ADMINISTRATION

For external use only

Keep out of reach of children.